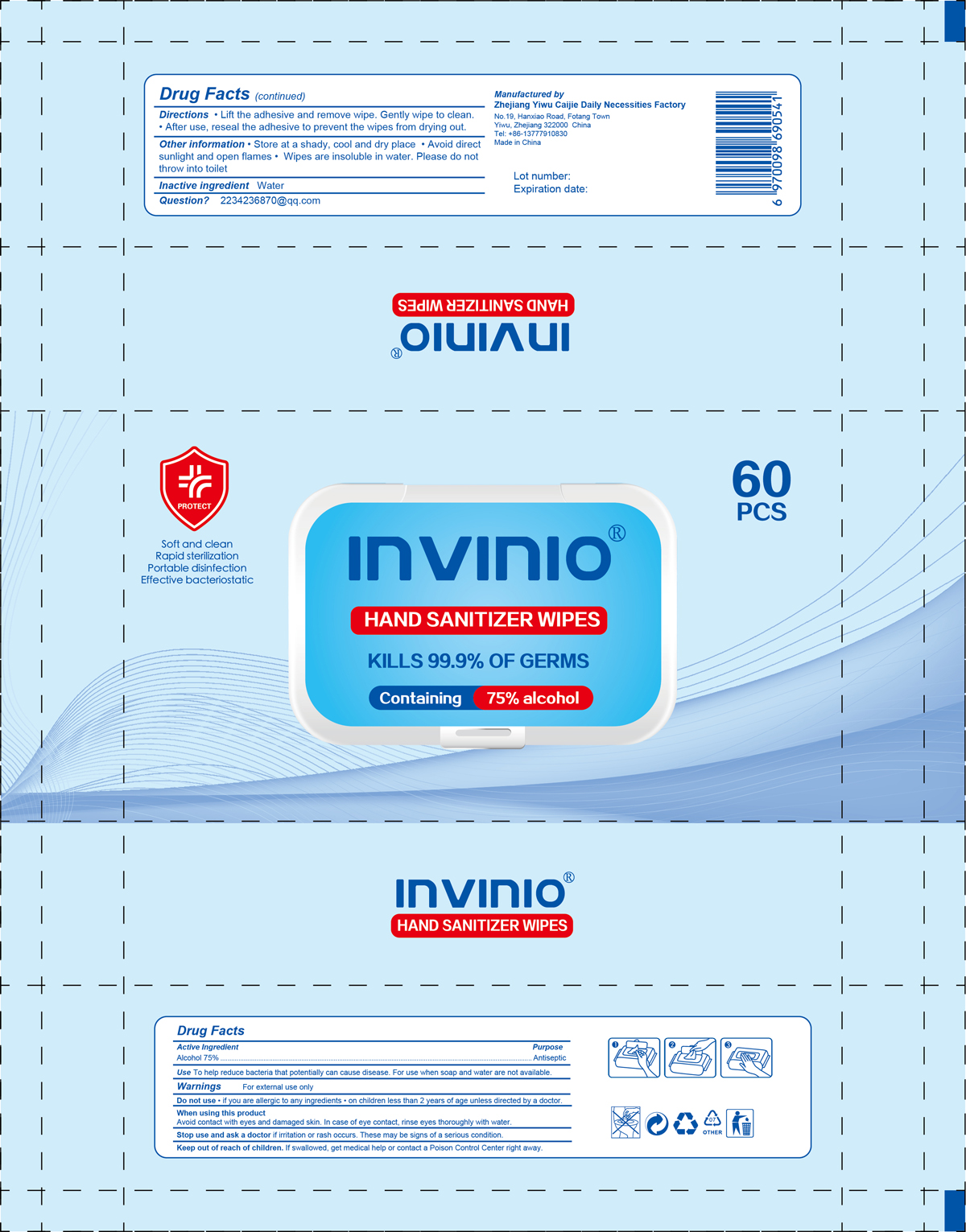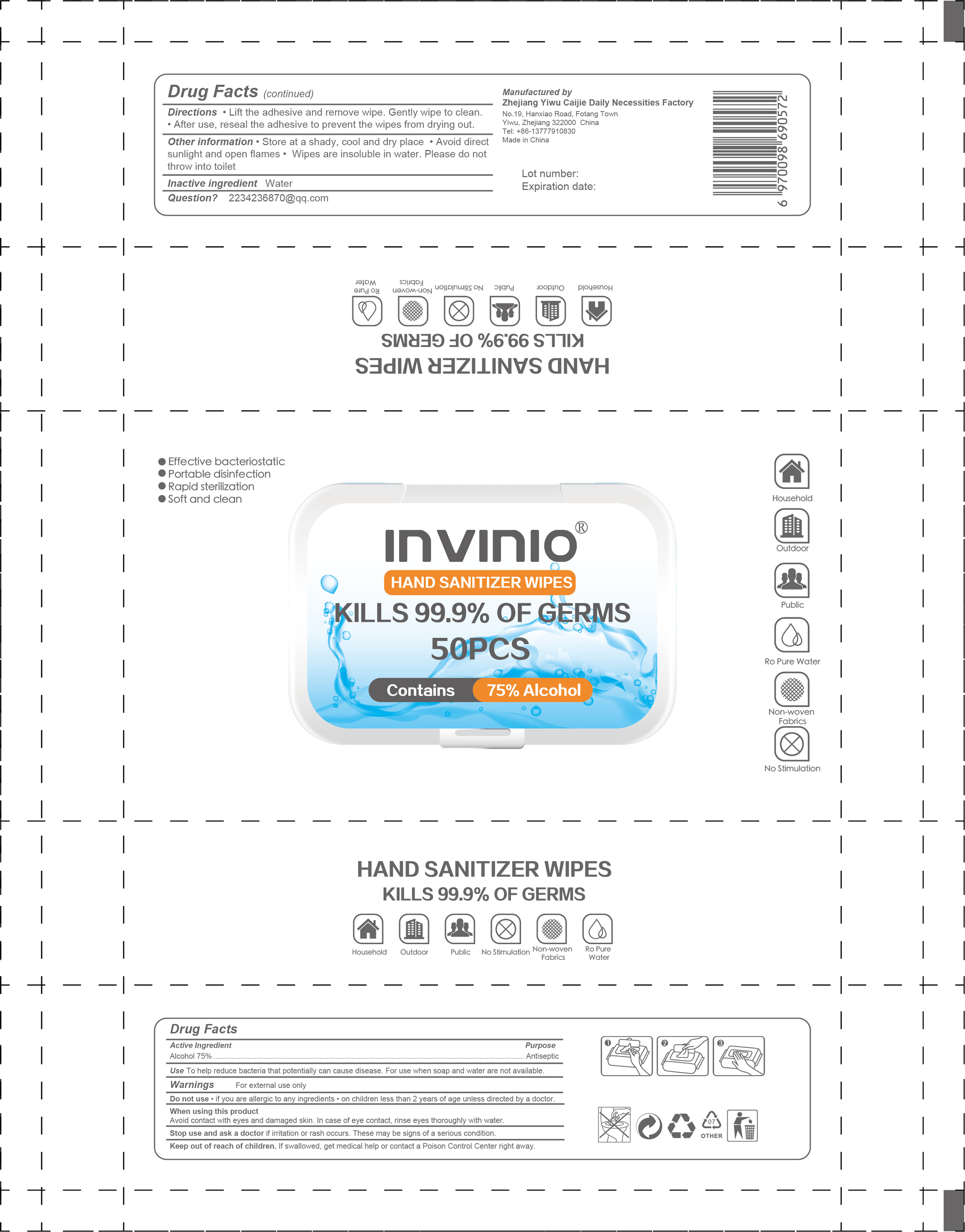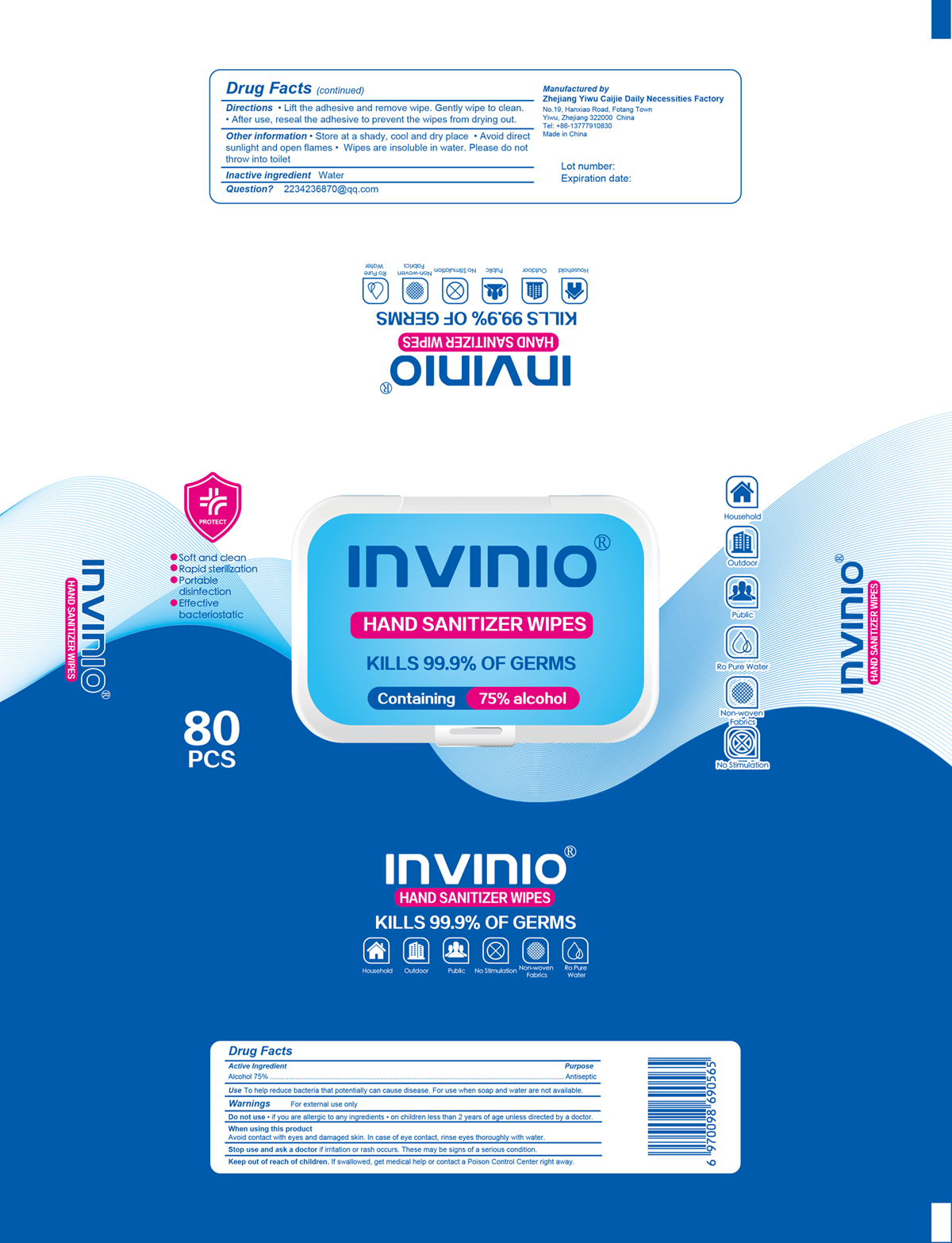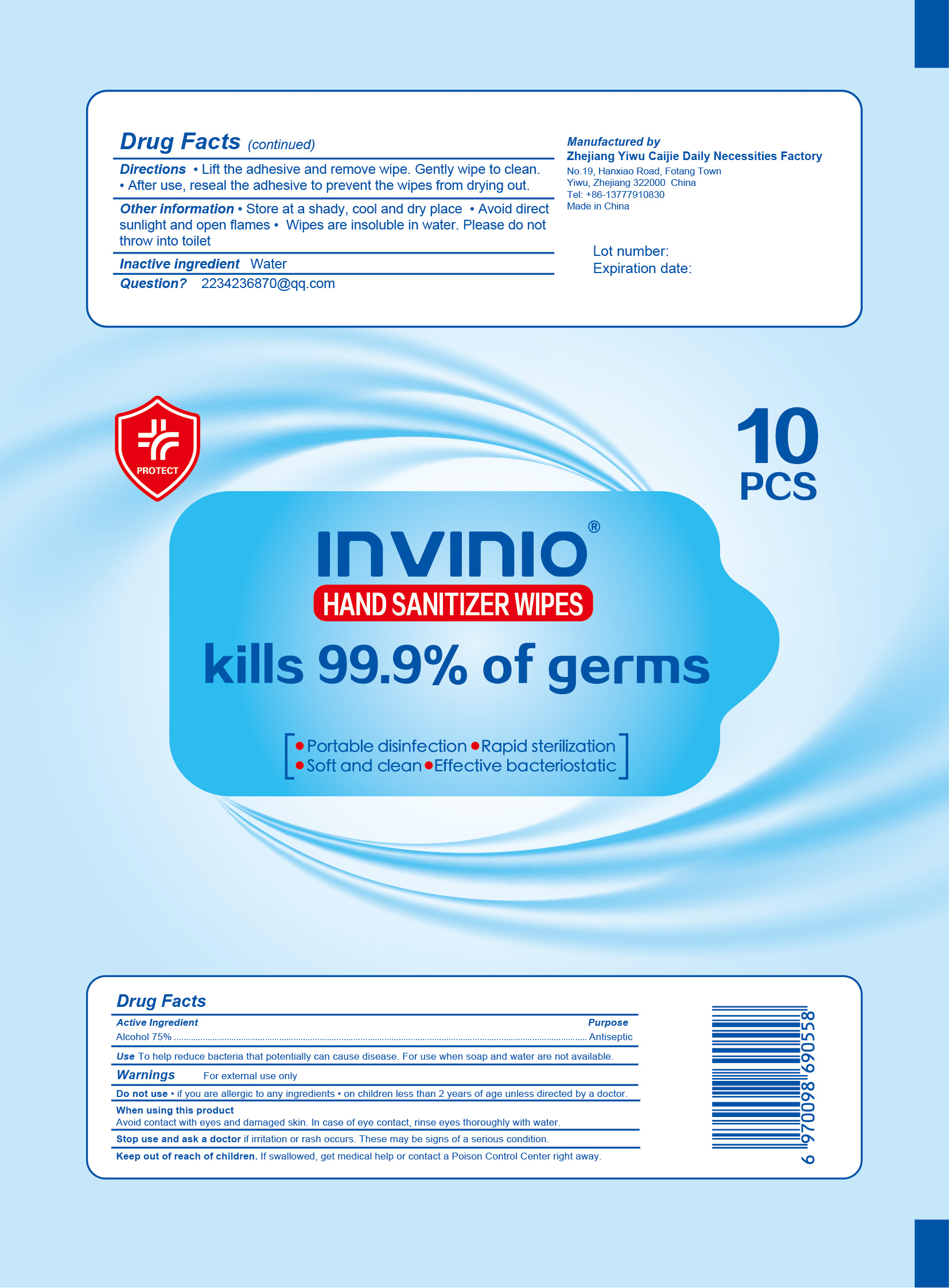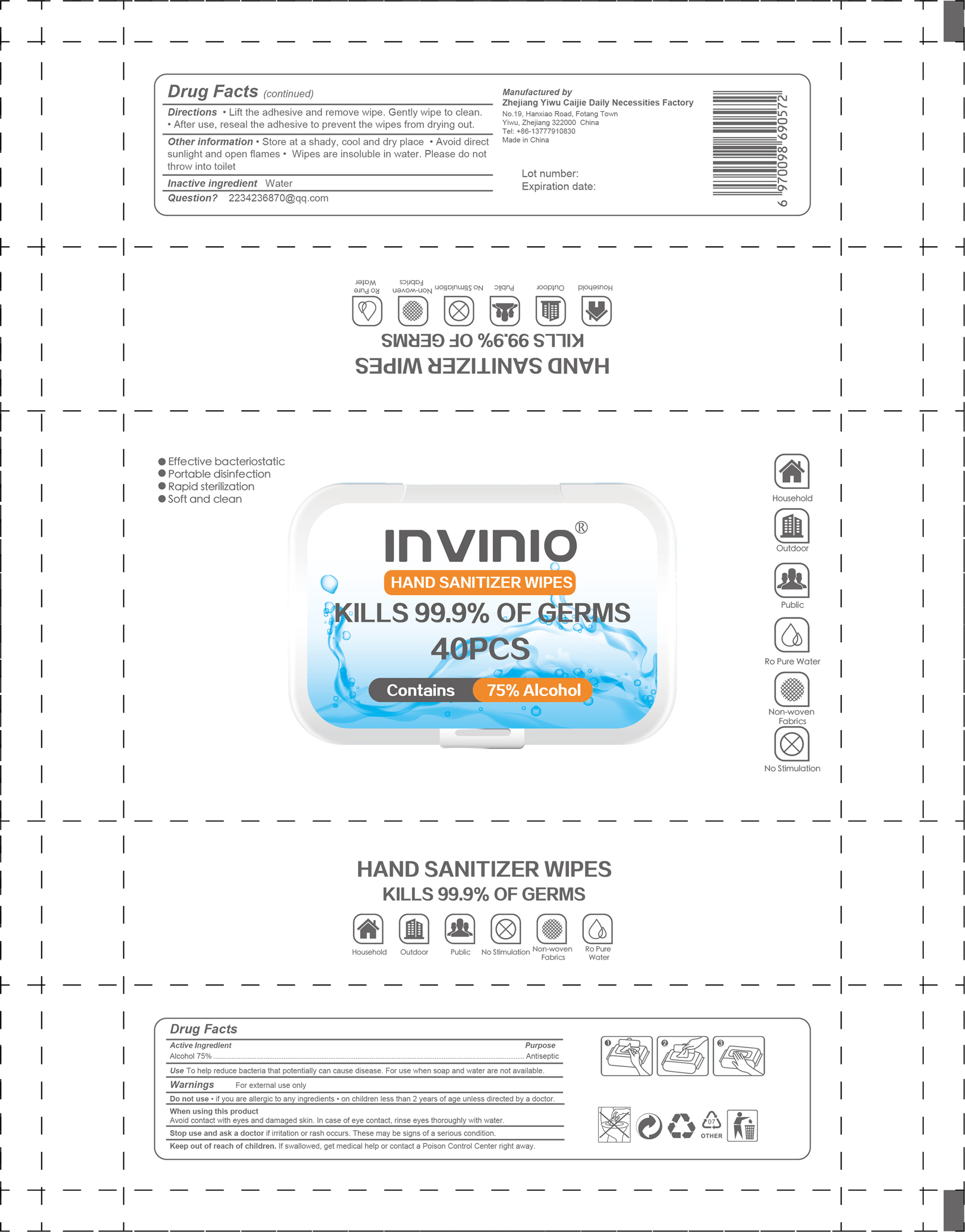 DRUG LABEL: Hand Sanitizer wipes
NDC: 78150-001 | Form: CLOTH
Manufacturer: Zhejiang Yiwu Caijie Daily Necessities Factory
Category: otc | Type: HUMAN OTC DRUG LABEL
Date: 20200722

ACTIVE INGREDIENTS: ALCOHOL 75 mL/100 g
INACTIVE INGREDIENTS: WATER

Hand sanitizer wipes

Active Ingredient(s)

Alcohol 75%. Purpose: Antiseptic

Purpose

Antiseptic, Hand Sanitizer wipes

Use

To help reduce bacteria that potentially can cause disease. For use when soap and water are not available.

Warnings

For external use only.

Do not use

- if you are allergic to any ingredients
- on children less than 2 years of age unless directed by a doctor

When using this product

Avoid contact with eyes and damaged skin. In case of eye contact, rinse eyes throughly with water

Stop use and ask a doctor

if irritation or rash occurs. These may be signs of a serious condition.

Keep out of reach of children. If swallowed, get medical help or contact a Poison Control Center right away.

Directions

- Lift the adhesive and remove wipe. Gently wipe to clean.
- After use, reseal the adhesive to prevent the wipes from drying out.

Other information

- Store at a shady, cool and dry place.
- Avoid direct sunlight and open flames.
- Wipes are insoluble in water. Please do not throw into toilet.

Inactive ingredients

water

Package Label - Principal Display Panel

60 PCS NDC: 78150-001-01

50 PCS NDC: 78150-001-02

80 PCS NDC: 78150-001-03

10 PCS NDC: 78150-001-04

40 PCS NDC: 78150-001-05